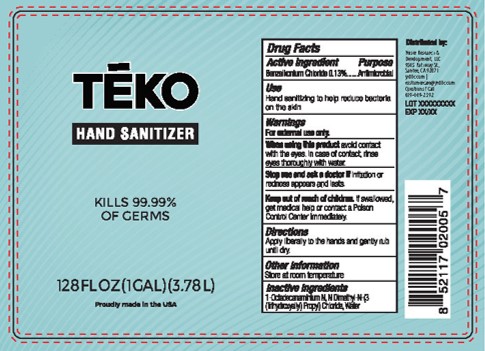 DRUG LABEL: All Day Hand Sanitizer
NDC: 79039-300 | Form: LIQUID
Manufacturer: BPI Packaging, LLC
Category: otc | Type: HUMAN OTC DRUG LABEL
Date: 20200625

ACTIVE INGREDIENTS: BENZALKONIUM CHLORIDE 0.13 g/1 mL
INACTIVE INGREDIENTS: WATER; ALCOHOL

Active Ingredient Purpose

Benzalkonium Chloride 0.13%...Antimicrobial

PURPOSE

Antimicrobial

Dosage and Administration

Directioins: Apply liberally to the hands and gently rub ubtil dry

Warnings

For External use Only.

When Using this product avoid contact with the eyes. In case of contact, rinse eyes thoroughly with water.

Stop use and ask a doctor if irritation or redness appears and lasts.

Keep out of reach of children. If swallowed, get medical help or contact a Pioson Control Center immediately.

Directions

Apply liberally to the hands and gently rub until dry.

Other Information

Store at room temperature

Inactive Ingredients

1-Octadecanaminium N, N Dimethyl-N-(3(Trihydroxysilyl) Propyl) Chloride, Water